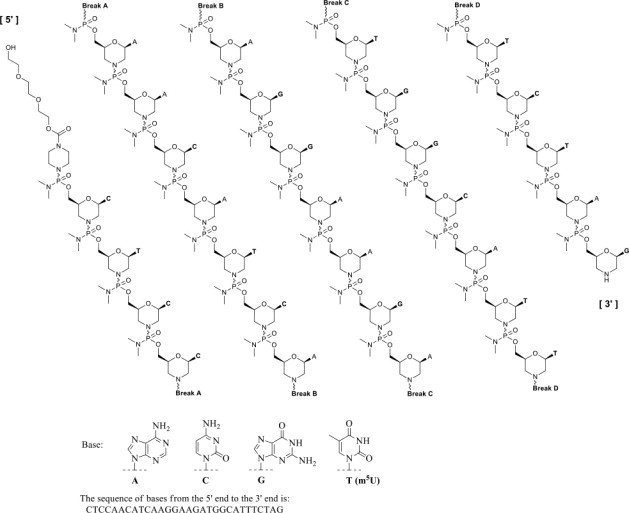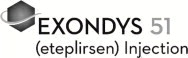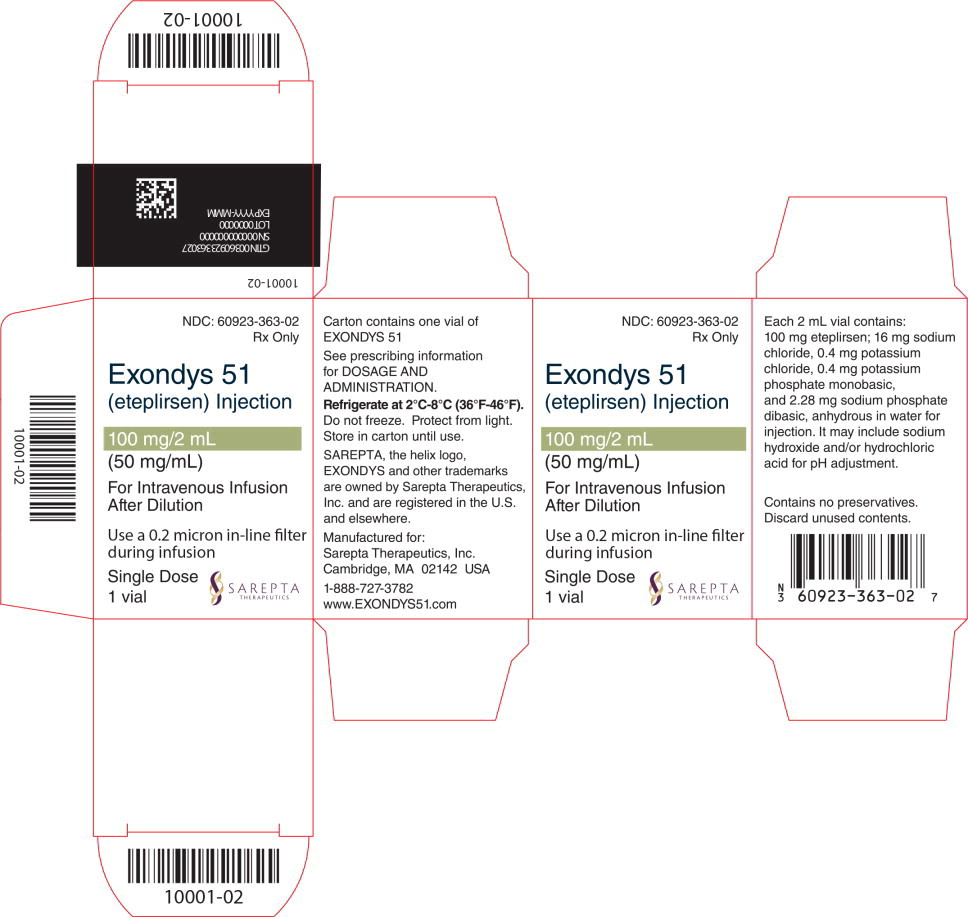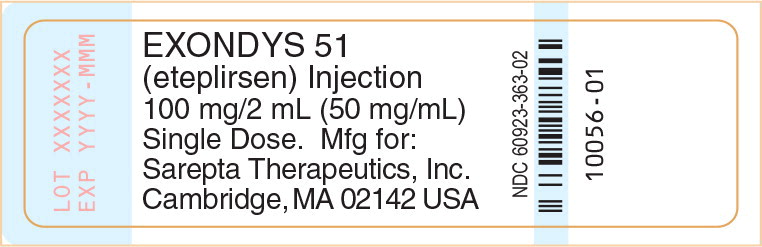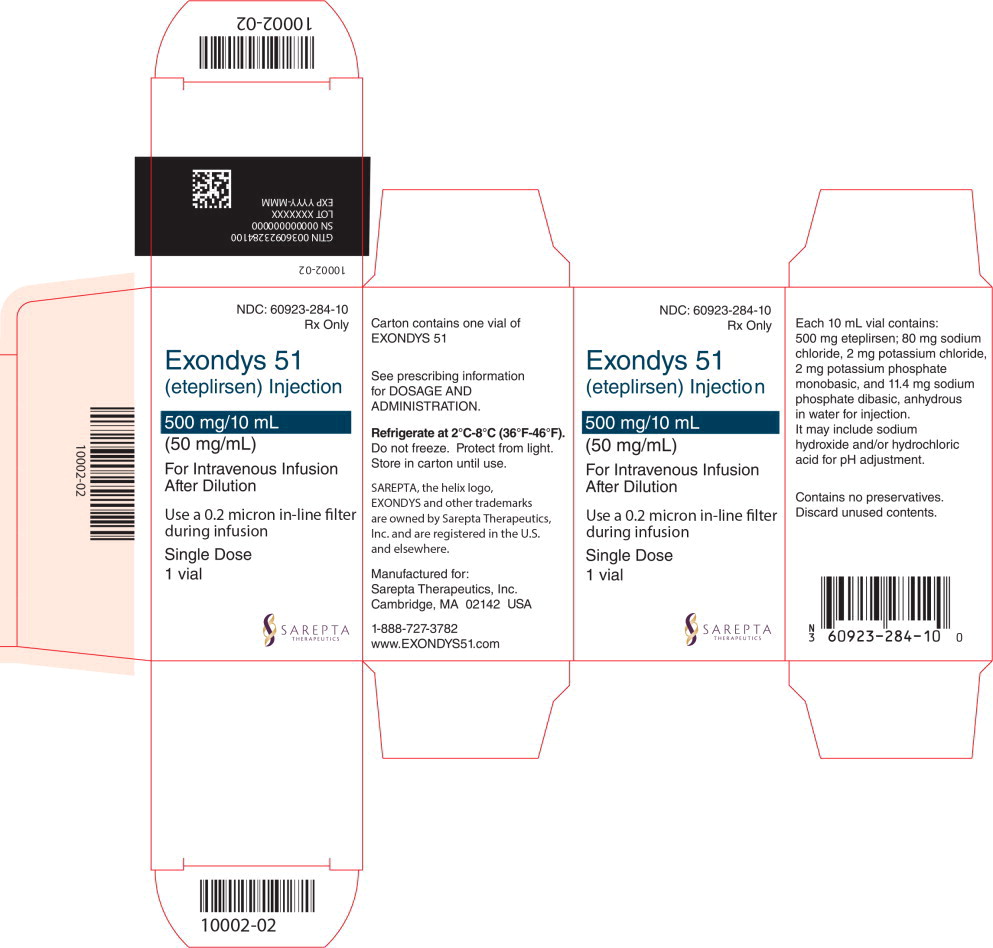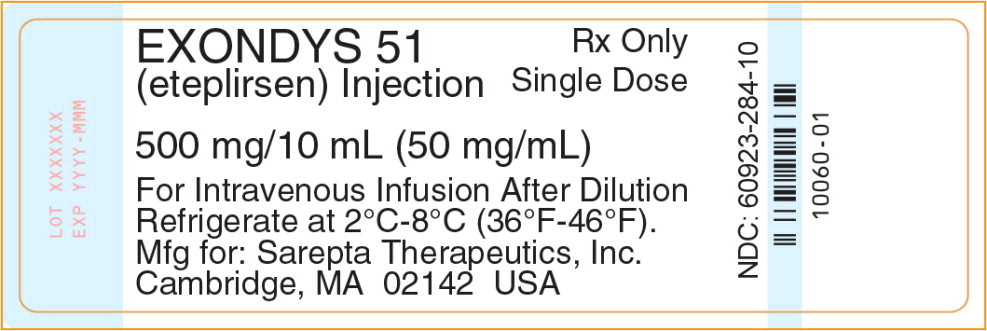 DRUG LABEL: Exondys 51
NDC: 60923-363 | Form: INJECTION
Manufacturer: Sarepta Therapeutics, Inc.
Category: prescription | Type: HUMAN PRESCRIPTION DRUG LABEL
Date: 20250813

ACTIVE INGREDIENTS: eteplirsen 50 mg/1 mL
INACTIVE INGREDIENTS: sodium chloride; potassium chloride; potassium phosphate, monobasic; sodium phosphate, dibasic, anhydrous; sodium hydroxide; hydrochloric acid; water

HIGHLIGHTS OF PRESCRIBING INFORMATION

These highlights do not include all the information needed to use EXONDYS 51® safely and effectively. See full prescribing information for EXONDYS 51.
EXONDYS 51 (eteplirsen) injection, for intravenous use
Initial U.S. Approval: 2016

RECENT MAJOR CHANGES

Dosage and Administration (2.2) | 08/2025

1 INDICATIONS AND USAGE

EXONDYS 51 is an antisense oligonucleotide indicated for the treatment of Duchenne muscular dystrophy (DMD) in patients who have a confirmed mutation of the DMD gene that is amenable to exon 51 skipping. This indication is approved under accelerated approval based on an increase in dystrophin in skeletal muscle observed in some patients treated with EXONDYS 51 [see Clinical Studies (14)]. Continued approval for this indication may be contingent upon verification of a clinical benefit in confirmatory trials. (1)

2 DOSAGE AND ADMINISTRATION

- 30 milligrams per kilogram of body weight once weekly (2.1)
- Administer as an intravenous infusion over 35 to 60 minutes via an in-line 0.2 micron filter (2.1, 2.3)
- Dilution required prior to administration (2.2)

3 DOSAGE FORMS AND STRENGTHS

Injection:

- 100 mg/2 mL (50 mg/mL) in single-dose vial (3)
- 500 mg/10 mL (50 mg/mL) in single-dose vial (3)

4 CONTRAINDICATIONS

None (4)

5 WARNINGS AND PRECAUTIONS

- Hypersensitivity Reactions: Hypersensitivity reactions, including bronchospasm, chest pain, cough, tachycardia, and urticaria, have occurred in patients treated with EXONDYS 51. If hypersensitivity reactions occur, institute appropriate medical treatment and consider slowing the infusion or interrupting the EXONDYS 51 therapy. (2.3, 5.1)

6 ADVERSE REACTIONS

The most common adverse reactions (incidence ≥35% and higher than placebo) were balance disorder and vomiting (6.1)

To report SUSPECTED ADVERSE REACTIONS, contact Sarepta Therapeutics, Inc. at 1-888-SAREPTA (1-888-727-3782) or FDA at 1-800-FDA-1088 or www.fda.gov/medwatch.

FULL PRESCRIBING INFORMATION

1 INDICATIONS AND USAGE

EXONDYS 51 is indicated for the treatment of Duchenne muscular dystrophy (DMD) in patients who have a confirmed mutation of the DMD gene that is amenable to exon 51 skipping. This indication is approved under accelerated approval based on an increase in dystrophin in skeletal muscle observed in some patients treated with EXONDYS 51 [see Clinical Studies (14)]. Continued approval for this indication may be contingent upon verification of a clinical benefit in confirmatory trials.

2 DOSAGE AND ADMINISTRATION

2.1 Dosing Information

The recommended dose of EXONDYS 51 is 30 milligrams per kilogram administered once weekly as a 35 to 60 minute intravenous infusion via an in-line 0.2 micron filter.

If a dose of EXONDYS 51 is missed, it may be administered as soon as possible after the scheduled time.

2.2 Preparation Instructions

EXONDYS 51 is supplied in single-dose vials as a preservative-free concentrated solution that requires dilution prior to administration. Parenteral drug products should be inspected visually for particulate matter and discoloration prior to administration, whenever solution and container permit. Use aseptic technique.

1. Calculate the total dose of EXONDYS 51 to be administered based on the patient's weight and the recommended dose of 30 milligrams per kilogram. Determine the volume of EXONDYS 51 needed and the correct number of vials to supply the full calculated dose.
2. Allow vials to warm to room temperature. Mix the contents of each vial by gently inverting 2 or 3 times. Do not shake.
3. Visually inspect each vial of EXONDYS 51. EXONDYS 51 is a clear, colorless solution that may have some opalescence, and may contain white to off-white amorphous particles. Do not use if the solution in the vials is cloudy, discolored or contains extraneous particulate matter other than white to off-white amorphous particles.
4. With a syringe fitted with a 21-gauge or smaller non-coring needle, withdraw the calculated volume of EXONDYS 51 from the appropriate number of vials.
5. Dilute the withdrawn EXONDYS 51 in 0.9% Sodium Chloride Injection, USP, to make a total volume of 100-150 mL. Visually inspect the diluted solution. Do not use if the solution is cloudy, discolored or contains extraneous particulate matter other than white to off-white amorphous particles.
6. Administer the diluted solution via an in-line 0.2 micron filter.
7. EXONDYS 51 contains no preservatives and should be administered immediately after dilution. Complete infusion of diluted EXONDYS 51 solution within 8 hours of dilution. If immediate use is not possible, the diluted solution may be stored for up to 24 hours at 2ºC to 8ºC (36ºF to 46ºF). Do not freeze. Discard unused EXONDYS 51.

2.3 Administration Instructions

Application of a topical anesthetic cream to the infusion site prior to administration of EXONDYS 51 may be considered.

EXONDYS 51 is administered via intravenous infusion. Flush the intravenous access line with 0.9% Sodium Chloride Injection, USP, prior to and after infusion.

Infuse the diluted EXONDYS 51 solution over 35 to 60 minutes via an in-line 0.2 micron filter. Do not mix other medications with EXONDYS 51 or infuse other medications concomitantly via the same intravenous access line.

If a hypersensitivity reaction occurs, consider slowing the infusion or interrupting the EXONDYS 51 therapy [see Warnings and Precautions (5.1) and Adverse Reactions (6.1)].

3 DOSAGE FORMS AND STRENGTHS

EXONDYS 51 is a clear and colorless solution that may have some opalescence, and may contain white to off-white amorphous particles, and is available as follows:

- Injection: 100 mg/2 mL (50 mg/mL) solution in a single-dose vial
- Injection: 500 mg/10 mL (50 mg/mL) solution in a single-dose vial

4 CONTRAINDICATIONS

None.

5 WARNINGS AND PRECAUTIONS

5.1 Hypersensitivity Reactions

Hypersensitivity reactions, including bronchospasm, chest pain, cough, tachycardia, and urticaria, have occurred in patients who were treated with EXONDYS 51. If a hypersensitivity reaction occurs, institute appropriate medical treatment and consider slowing the infusion or interrupting the EXONDYS 51 therapy [see Dosage and Administration (2.3)].

6 ADVERSE REACTIONS

6.1 Clinical Trials Experience

Because clinical trials are conducted under widely varying conditions, adverse reaction rates observed in clinical trials of a drug cannot be directly compared to rates in the clinical trials of another drug and may not reflect the rates observed in practice.

EXONDYS 51 was studied in a double-blind, placebo-controlled study for 24 weeks (Study 1), followed by an open label extension (Study 2). In Study 1, 12 patients were randomized to receive weekly intravenous infusions of EXONDYS 51 (n=8) or placebo (n=4) for 24 weeks. All 12 patients continued in Study 2 and received open-label EXONDYS 51 weekly for up to 208 weeks.

In Study 1, 4 patients received placebo, 4 patients received EXONDYS 51 30 mg/kg, and 4 patients received EXONDYS 51 50 mg/kg (1.7 times the recommended dosage). In Study 2, 6 patients received EXONDYS 51 30 mg/kg/week and 6 patients received EXONDYS 51 50 mg/kg/week [see Clinical Studies (14)].

Adverse reactions that occurred in 2 or more patients who received EXONDYS 51 and were more frequent than in the placebo group in Study 1 are presented in Table 1 (the 30 and 50 mg/kg groups are pooled). Because of the small numbers of patients, these represent crude frequencies that may not reflect the frequencies observed in practice. The 50 mg/kg once weekly dosing regimen of EXONDYS 51 is not recommended [see Dosage and Administration (2.1)].

The most common adverse reactions were balance disorder and vomiting.

Table 1. Adverse Reactions in DMD Patients Treated with 30 or 50 mg/kg/week^1 EXONDYS 51 with Incidence at Least 25% More than Placebo (Study 1)
Adverse Reactions | EXONDYS 51 (N=8) | Placebo (N=4)
 | % | %
Balance disorder | 38 | 0
Vomiting | 38 | 0
Contact dermatitis | 25 | 0
^1 50 mg/kg/week = 1.7 times the recommended dosage

Adverse Reactions from Observational Clinical Studies

The following adverse reactions have been identified during observational studies that were conducted as part of the clinical development program and continued postapproval.

In open-label observational studies, 163 patients received at least one intravenous dose of EXONDYS 51, with doses ranging between 0.5 mg/kg (0.017 times the recommended dosage) and 50 mg/kg (1.7 times the recommended dosage). All patients were male and had genetically confirmed Duchenne muscular dystrophy. Age at study entry was 6 months to 19 years. Most (85%) patients were Caucasian.

The most common adverse reactions seen in greater than 10% of the study population were headache, cough, rash, and vomiting.

Hypersensitivity reactions have occurred in patients treated with EXONDYS 51 [see Warnings and Precautions (5.1)].

6.2 Postmarketing Experience

The following adverse reactions have been identified during postapproval use of EXONDYS 51. Because these reactions are reported voluntarily from a population of uncertain size, it is not always possible to reliably estimate their frequency or establish a causal relationship to drug exposure.

Postmarketing adverse reactions that occurred during infusion include bronchospasm, cyanosis of the lips, and malaise. The following adverse reactions have also been reported in patients receiving EXONDYS 51: pyrexia, flushing, protein urine present, and dehydration.

8 USE IN SPECIFIC POPULATIONS

8.1 Pregnancy

Risk Summary

There are no human or animal data available to assess the use of EXONDYS 51 during pregnancy. In the U.S. general population, major birth defects occur in 2 to 4% and miscarriage occurs in 15 to 20% of clinically recognized pregnancies.

8.2 Lactation

Risk Summary

There are no human or animal data to assess the effect of EXONDYS 51 on milk production, the presence of eteplirsen in milk, or the effects of EXONDYS 51 on the breastfed infant.

The developmental and health benefits of breastfeeding should be considered along with the mother's clinical need for EXONDYS 51 and any potential adverse effects on the breastfed infant from EXONDYS 51 or from the underlying maternal condition.

8.4 Pediatric Use

EXONDYS 51 is indicated for the treatment of Duchenne muscular dystrophy (DMD) in patients who have a confirmed mutation of the DMD gene that is amenable to exon 51 skipping, including pediatric patients [see Clinical Studies (14)].

Intravenous administration of eteplirsen (0, 100, 300, or 900 mg/kg) to juvenile male rats once weekly for 10 weeks beginning on postnatal day 14 resulted in renal tubular necrosis at the highest dose tested and decreased bone densitometry parameters (mineral density, mineral content, area) at all doses. The kidney findings were associated with clinical pathology changes (increased serum urea nitrogen and creatinine, decreased urine creatinine clearance). No effects were observed on the male reproductive system, neurobehavioral development, or immune function. An overall no-effect dose was not identified. Plasma eteplirsen exposure (AUC) at the lowest dose tested (100 mg/kg) was similar to that in humans at the recommended human dose (30 mg/kg).

8.5 Geriatric Use

DMD is largely a disease of children and young adults; therefore, there is no geriatric experience with EXONDYS 51.

8.6 Patients with Renal Impairment

Renal clearance of eteplirsen is reduced in non-DMD adults with renal impairment based on estimated creatinine clearance [see Clinical Pharmacology (12.3)]. However, because of the effect of reduced skeletal muscle mass on creatinine measurements in DMD patients, no specific dosage adjustment can be recommended for DMD patients with renal impairment.

11 DESCRIPTION

EXONDYS 51 (eteplirsen) injection is a sterile, aqueous, preservative-free, concentrated solution for dilution prior to intravenous administration. EXONDYS 51 is clear and colorless, and may have some opalescence, and may contain white to off-white amorphous particles. EXONDYS 51 is supplied in single dose vials containing 100 mg or 500 mg eteplirsen (50 mg/mL). EXONDYS 51 is formulated as an isotonic, phosphate buffered saline solution with an osmolality of 260 to 320 mOsm and a pH of 7.5. Each milliliter of EXONDYS 51 contains 50 mg eteplirsen; 0.2 mg potassium chloride, 0.2 mg potassium phosphate monobasic, 8 mg sodium chloride, and 1.14 mg sodium phosphate dibasic, anhydrous, in water for injection. The product may contain hydrochloric acid or sodium hydroxide to adjust pH.

Eteplirsen is an antisense oligonucleotide of the phosphorodiamidate morpholino oligomer (PMO) subclass. PMOs are synthetic molecules in which the five-membered ribofuranosyl rings found in natural DNA and RNA are replaced by a six-membered morpholino ring. Each morpholino ring is linked through an uncharged phosphorodiamidate moiety rather than the negatively charged phosphate linkage that is present in natural DNA and RNA. Each phosphorodiamidate morpholino subunit contains one of the heterocyclic bases found in DNA (adenine, cytosine, guanine, or thymine). Eteplirsen contains 30 linked subunits. The molecular formula of eteplirsen is C364H569N177O122P30 and the molecular weight is 10305.7 daltons.

The structure and base sequence of eteplirsen are:

12 CLINICAL PHARMACOLOGY

12.1 Mechanism of Action

Eteplirsen is designed to bind to exon 51 of dystrophin pre-mRNA, resulting in exclusion of this exon during mRNA processing in patients with genetic mutations that are amenable to exon 51 skipping. Exon skipping is intended to allow for production of an internally truncated dystrophin protein, which was evaluated in Study 2 and Study 3 [see Clinical Studies (14)].

12.2 Pharmacodynamics

All EXONDYS 51-treated patients evaluated (n=36) were found to produce messenger ribonucleic acid (mRNA) for a truncated dystrophin protein by reverse transcription polymerase chain reaction.

In Study 2, the average dystrophin protein level in muscle tissue after 180 weeks of treatment with EXONDYS 51 was 0.93% of normal (i.e., 0.93% of the dystrophin level in healthy subjects). Because of insufficient information on dystrophin protein levels before treatment with EXONDYS 51 in Study 1, it is not possible to estimate dystrophin production in response to EXONDYS 51 in Study 1.

In Study 3, the average dystrophin protein level was 0.16% of normal before treatment, and 0.44% of normal after 48 weeks of treatment with EXONDYS 51 [see Clinical Studies (14)]. The median increase in truncated dystrophin in Study 3 was 0.1% [see Clinical Studies (14)].

Dystrophin levels assessed by western blot can be meaningfully influenced by differences in sample processing, analytical technique, reference materials, and quantitation methodologies. Therefore, comparing dystrophin results from different assay protocols will require a standardized reference material and additional bridging studies.

12.3 Pharmacokinetics

Following single or multiple intravenous infusions of EXONDYS 51 in male pediatric DMD patients, plasma concentration-time profiles of eteplirsen were generally similar and showed multi-phasic decline. The majority of drug elimination occurred within 24 hours. Approximate dose-proportionality and linearity in PK properties were observed following multiple-dose studies (0.5 mg/kg/week [0.017 times the recommended dosage] to 50 mg/kg/week [1.7 times the recommended dosage]). There was no significant drug accumulation following weekly dosing across this dose range. The inter-subject variability for eteplirsen Cmax and AUC range from 20 to 55%.

Following single or multiple intravenous infusions of EXONDYS 51, the peak plasma concentrations (Cmax) of eteplirsen occurred near the end of infusion (i.e., 1.1 to 1.2 hours across a dose range of 0.5 mg/kg/week to 50 mg/kg/week).

Distribution

In vitro investigation suggested that plasma protein binding of eteplirsen in human ranges between 6 to 17%. The mean apparent volume of distribution (Vss) of eteplirsen was 600 mL/kg following weekly intravenous infusion of EXONDYS 51 at 30 mg/kg.

Twenty-four hours after the end of the infusion, mean concentrations of eteplirsen were 0.07% of Cmax. Accumulation of eteplirsen during once weekly dosing has not been observed.

Elimination

The total clearance of eteplirsen was 339 mL/hr/kg following 12 weeks of therapy with 30 mg/kg/week.

Metabolism

Eteplirsen did not appear to be metabolized by hepatic microsomes of any species tested, including humans.

Excretion

Renal clearance of eteplirsen accounts for approximately two-thirds of the administered dose within 24 hours of intravenous administration. Elimination half-life (t1/2) of eteplirsen was 3 to 4 hours.

Specific Populations

Age:

The pharmacokinetics of eteplirsen have been evaluated in male pediatric DMD patients. There is no experience with the use of EXONDYS 51 in patients 65 years of age or older.

Sex:

Sex effects have not been evaluated; EXONDYS 51 has not been studied in female patients.

Race:

Potential impact of race is not known because 89% of the patients in studies were Caucasians.

Patients with Renal Impairment:

The effect of renal impairment on the pharmacokinetics of eteplirsen was evaluated in non-DMD subjects aged 51 to 75 years with mild (n=8, creatinine clearance ≥60 mL/min and <90 mL/min) or moderate (n=8, creatinine clearance ≥30 mL/min and <60 mL/min) renal impairment and matched healthy subjects (n=9, creatinine clearance >90 mL/min). Subjects received a single 30 mg/kg intravenous dose of eteplirsen.

Subjects with mild and moderate renal impairment showed higher eteplirsen exposure compared to subjects with normal renal function. In subjects with mild and moderate renal impairment, exposure (AUC) increased approximately 1.4-fold and 2.4-fold, respectively. The effect of severe renal impairment or end-stage renal disease on eteplirsen pharmacokinetics and safety has not been studied.

Estimated creatinine clearance values derived from the Cockcroft-Gault equation and the threshold definitions for mild, moderate, and severe renal impairment in otherwise healthy adults would not be generalizable to patients with DMD. Therefore, no specific dosage adjustment can be recommended for patients with renal impairment.

Patients with Hepatic Impairment:

EXONDYS 51 has not been studied in patients with hepatic impairment.

Drug Interaction Studies

In vitro data showed that eteplirsen did not significantly inhibit CYP1A2, CYP2B6, CYP2C8, CYP2C9, CYP2C19, CYP2D6, or CYP3A4/5. Eteplirsen did not induce CYP2B6 or CYP3A4, and induction of CYP1A2 was substantially less than the prototypical inducer, omeprazole. Eteplirsen was not a substrate nor did it have any major inhibitory potential for any of the key human transporters tested (OAT1, OAT3, OCT1, OCT2, OATP1B1, OATP1B3, P-gp, BCRP, MRP2 and BSEP). Based on in vitro data on plasma protein binding, CYP or drug transporter interactions, and microsomal metabolism, eteplirsen is expected to have a low potential for drug-drug interactions in humans.

12.6 Immunogenicity

The observed incidence of anti-drug antibodies (ADA) is highly dependent on the sensitivity and specificity of the assay. Differences in assay methods preclude meaningful comparisons of the incidence of ADA in the studies described below with the incidence of ADA in other studies, including those of eteplirsen.

With administration of 30 mg/kg/week of EXONDYS 51, during the 192-week treatment duration in three clinical studies, 1 out of 129 patients (0.78%) was positive for anti-eteplirsen IgG and 3 out of 21 patients with non-missing samples (14.3%) were positive for anti-eteplirsen IgE. Because of the low occurrence of anti-eteplirsen antibodies, the impact of immunogenicity status on the dystrophin levels, pharmacokinetics, pharmacodynamics, safety, and/or efficacy of EXONDYS 51 is unknown.

13 NONCLINICAL TOXICOLOGY

13.1 Carcinogenesis, Mutagenesis, Impairment of Fertility

Carcinogenesis

Administration of eteplirsen to male transgenic (Tg.rasH2) mice (0, 200, 500, or 960 mg/kg) weekly for 26 weeks (intravenous [IV] injection for 15 weeks, followed by subcutaneous injection for 11 weeks) and to male rats (0, 60, 180, or 600 mg/kg IV) weekly for 96 weeks resulted in no increase in neoplasms.

Mutagenesis

Eteplirsen was negative in in vitro (bacterial reverse mutation and chromosomal aberration in CHO cells) and in vivo (mouse bone marrow micronucleus) assays.

Impairment of Fertility

Fertility studies in animals were not conducted with eteplirsen. No effects on the male reproductive system were observed following intravenous administration of eteplirsen (0, 5, 40, or 320 mg/kg) to male monkeys once weekly for 39 weeks. Plasma eteplirsen exposure (AUC) in monkeys at the highest dose tested was 20 times that in humans at recommended human dose (30 mg/kg).

14 CLINICAL STUDIES

EXONDYS 51 was evaluated in three clinical studies in patients who have a confirmed mutation of the DMD gene that is amenable to exon 51 skipping.

In Study 1, patients were randomized to receive weekly infusions of EXONDYS 51 (30 mg/kg, n=4); EXONDYS 51 (50 mg/kg, n=4), or placebo (n=4) for 24 weeks. The primary endpoint was dystrophin production; a clinical outcome measure, the 6-minute walk test (6MWT), was also assessed. The 6MWT measures the distance that a patient can walk on a flat, hard surface in a period of 6 minutes. Patients had a mean age of 9.4 years, a mean 6-minute walk distance (6MWD) at baseline of 363 meters, and were on a stable dose of corticosteroids for at least 6 months. There was no significant difference in change in 6MWD between patients treated with EXONDYS 51 and those treated with placebo.

All 12 patients who participated in Study 1 continued treatment with open-label EXONDYS 51 weekly for an additional 4 years in Study 2. The 4 patients who had been randomized to placebo were re-randomized 1:1 to EXONDYS 51 30 or 50 mg/kg/week such that there were 6 patients on each dose. Patients who participated in Study 2 were compared to an external control group. The primary clinical efficacy outcome measure was the 6MWT. Eleven patients in Study 2 had a muscle biopsy after 180 weeks of treatment with EXONDYS 51, which was analyzed for dystrophin protein level by Sarepta western blot. Study 2 failed to provide evidence of a clinical benefit of EXONDYS 51 compared to the external control group. The average dystrophin protein level after 180 weeks of treatment with EXONDYS 51 was 0.93% of the dystrophin level in healthy subjects. Because of insufficient information on dystrophin protein levels before treatment with EXONDYS 51 in Study 1, it is not possible to estimate dystrophin production in response to EXONDYS 51 in Study 1.

In Study 3, 13 patients were treated with open-label EXONDYS 51 (30 mg/kg) weekly for 48 weeks and had a muscle biopsy at baseline and after 48 weeks of treatment. Patients had a mean age of 8.9 years and were on a stable dose of corticosteroids for at least 6 months. Dystrophin levels in muscle tissue were assessed by Western blot. In the 12 patients with evaluable results, the pre-treatment dystrophin level was 0.16% ± 0.12% (mean ± standard deviation) of the dystrophin level in a healthy subject and 0.44% ± 0.43% after 48 weeks of treatment with EXONDYS 51 (p < 0.05). The median increase after 48 weeks was 0.1%.

Individual patient dystrophin levels from Study 3 are shown in Table 2.

Table 2. Sarepta Western Blot Results: EXONDYS 51-Treated (Week 48) vs Pre-treatment Baseline (% Normal Dystrophin) (Study 301)
Patient Number | Baseline % normal dystrophin | Week 48 % normal dystrophin | Change from Baseline % normal dystrophin
1 | 0.13 | 0.26 | 0.13
2 | 0.35 | 0.36 | 0.01
3 | 0.06 | 0.37 | 0.31
4 | 0.04 | 0.10 | 0.06
5 | 0.17 | 1.02 | 0.85
6 | 0.37 | 0.30 | -0.07
7 | 0.17 | 0.42 | 0.25
8 | 0.24 | 1.57 | 1.33
9 | 0.11 | 0.12 | 0.01
10 | 0.05 | 0.47 | 0.43
11 | 0.02 | 0.09 | 0.07
12 | 0.18 | 0.21 | 0.03
Mean | 0.16 | 0.44 | 0.28; p=0.008

16 HOW SUPPLIED/STORAGE AND HANDLING

16.1 How Supplied

EXONDYS 51 injection is supplied in single-dose vials. The solution is clear and colorless, and may have some opalescence, and may contain white to off-white amorphous particles.

- Single-dose vials containing 100 mg/2 mL (50 mg/mL) eteplirsen | NDC 60923-363-02
- Single-dose vials containing 500 mg/10 mL (50 mg/mL) eteplirsen | NDC 60923-284-10

16.2 Storage and Handling

Store EXONDYS 51 at 2°C to 8°C (36°F to 46°F). Do not freeze. Protect from light and store EXONDYS 51 in the original carton until ready for use.

17 PATIENT COUNSELING INFORMATION

Hypersensitivity Reactions

Advise patients and/or caregivers that symptoms of hypersensitivity, including bronchospasm, chest pain, cough, tachycardia, and urticaria can occur with EXONDYS 51. Instruct them to seek immediate medical care should they experience signs and symptoms of hypersensitivity [see Warnings and Precautions (5.1)].

Manufactured for:
Sarepta Therapeutics, Inc.
Cambridge, MA 02142 USA

SAREPTA, SAREPTA THERAPEUTICS, EXONDYS, EXONDYS 51, and the EXONDYS 51 Logo are trademarks of Sarepta Therapeutics, Inc. registered in the U.S. Patent and Trademark Office and may be registered in various other jurisdictions.

PACKAGE LABEL

Principal Display Panel – 100 mg/2 mL Carton Label

NDC: 60923-363-02

Rx Only

Exondys 51
(eteplirsen) Injection

100 mg/2 mL

(50 mg/mL)

For Intravenous Infusion
After Dilution

Use a 0.2 micron in-line filter
during infusion

Single Dose

1 vial

SAREPTA
THERAPEUTICS

PACKAGE LABEL

Principal Display Panel – 100 mg/2 mL Vial Label

NDC 60923-363-02

EXONDYS 51
(eterplirsen) Injection

100 mg/2 mL (50 mg/mL)

Single Dose. Mfg for:
Sarepta Therapeutics, Inc.

Cambridge, MA 02142 USA

PACKAGE LABEL

Principal Display Panel – 500 mg/10 mL Carton Label

NDC: 60923-284-10

Rx Only

Exondys 51
(eteplirsen) Injection

500 mg/10 mL

(50 mg/mL)

For Intravenous Infusion
After Dilution

Use a 0.2 micron in-line filter
during infusion

Single Dose

1 vial

SAREPTA
THERAPEUTICS

PACKAGE LABEL

Principal Display Panel – 500 mg/10 mL Vial Label

NDC 60923-284-10

EXONDYS 51
(eterplirsen) Injection

Rx Only
Single Dose

500 mg/10 mL (50 mg/mL)

For Intravenous Infusion After Dilution

Refrigerate at 2°C-8°C (36°F-46°F).

Mfg for: Sarepta Therapeutics, Inc.

Cambridge, MA 02142 USA